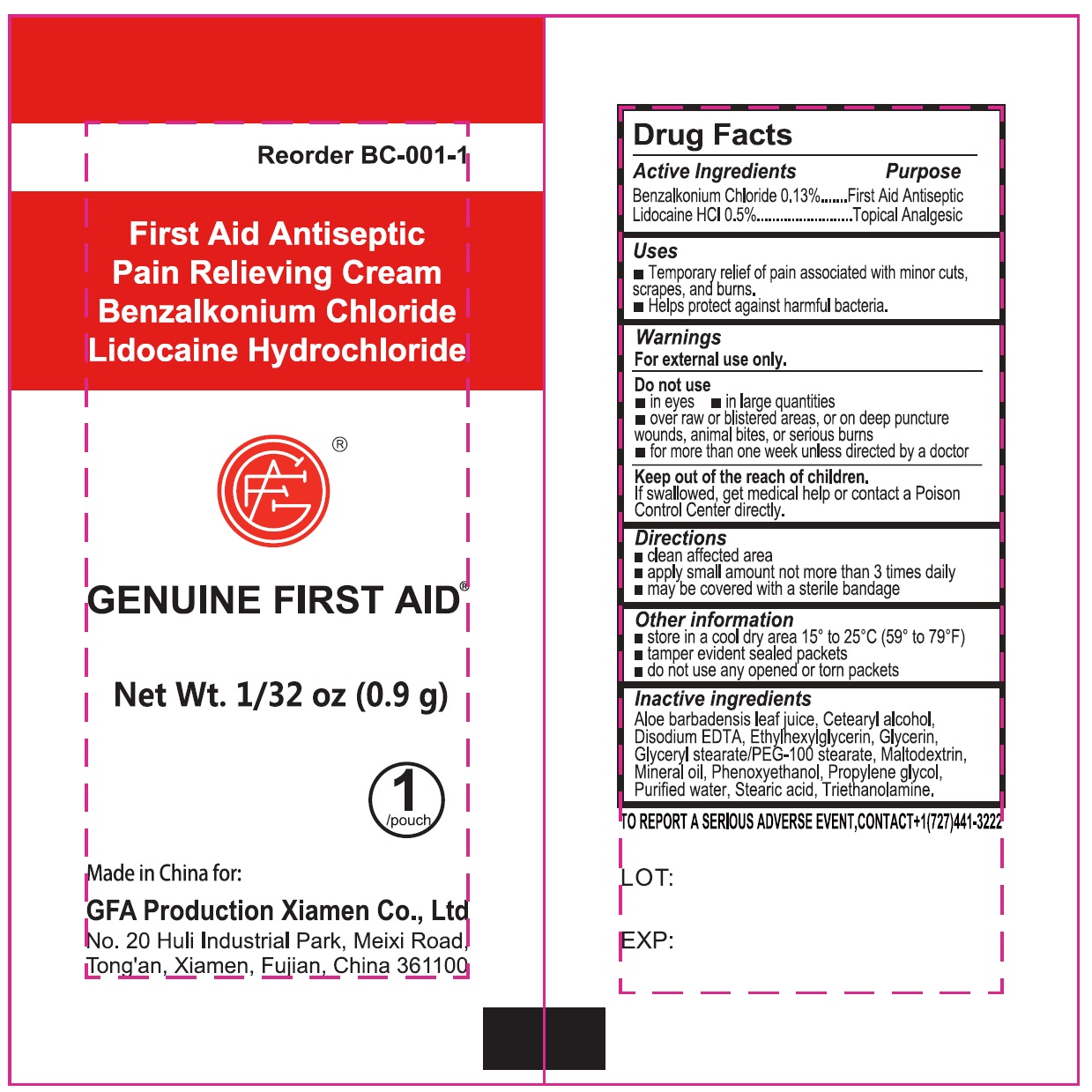 DRUG LABEL: Genuine First Aid Pain Relieving Cream
NDC: 50814-079 | Form: CREAM
Manufacturer: GFA Production (Xiamen) Co., Ltd.
Category: otc | Type: HUMAN OTC DRUG LABEL
Date: 20251107

ACTIVE INGREDIENTS: BENZALKONIUM CHLORIDE 1.3 mg/1 g; LIDOCAINE HYDROCHLORIDE 5 mg/1 g
INACTIVE INGREDIENTS: ALOE VERA LEAF; CETOSTEARYL ALCOHOL; EDETATE DISODIUM ANHYDROUS; ETHYLHEXYLGLYCERIN; GLYCERIN; GLYCERYL STEARATE/PEG-100 STEARATE; MALTODEXTRIN; MINERAL OIL; PHENOXYETHANOL; PROPYLENE GLYCOL; WATER; STEARIC ACID; TROLAMINE

Genuine First Aid Pain Relieving Cream

Active Ingredients

Benzalkonium Chloride 0.13%

Lidocaine HCl 0.5%

Purpose

First Aid Antiseptic

Topical Analgesic

Uses

- Temporary relief of pain associated with minor cuts, scrapes, and burns.
- Helps pretect against harmful bacteria.

Warnings

For external use only.

Do not use

• in eyes • in large quantities • over raw or blistered areas, or on deep puncture wounds, animal bites, or serious burns • for more than one week unless directed by a doctor

Keep out of the reach of children.

If swallowed, get medical help or contact a Poison Control Center directly.

Directions

- clean affected area
- apply small amount not more than 3 times daily
- may be covered with a sterile bandage

Other information

- store in a cool dry area 15° to 25° C (59° to 79°F)
- tamper evident sealed packets
- do not use any opened or torn packets

Inactive ingredients

Aloe Barbadensis Leaf Juice, Cetearyl Alcohol, Disodium EDTA, Ethylhexylglycerin, Glycerin, Glyceryl Stearate/PEG-100 Stearate, Maltodextrin, Mineral Oil, Phenoxyethanol, Propylene Glycol, Purified Water, Stearic Acid, Triethanolamine